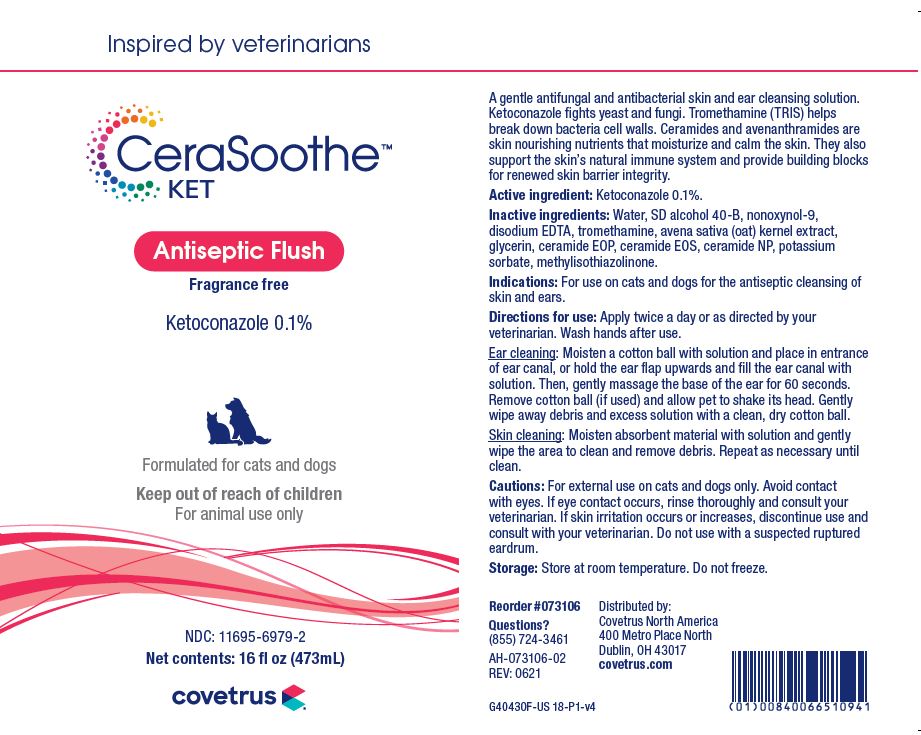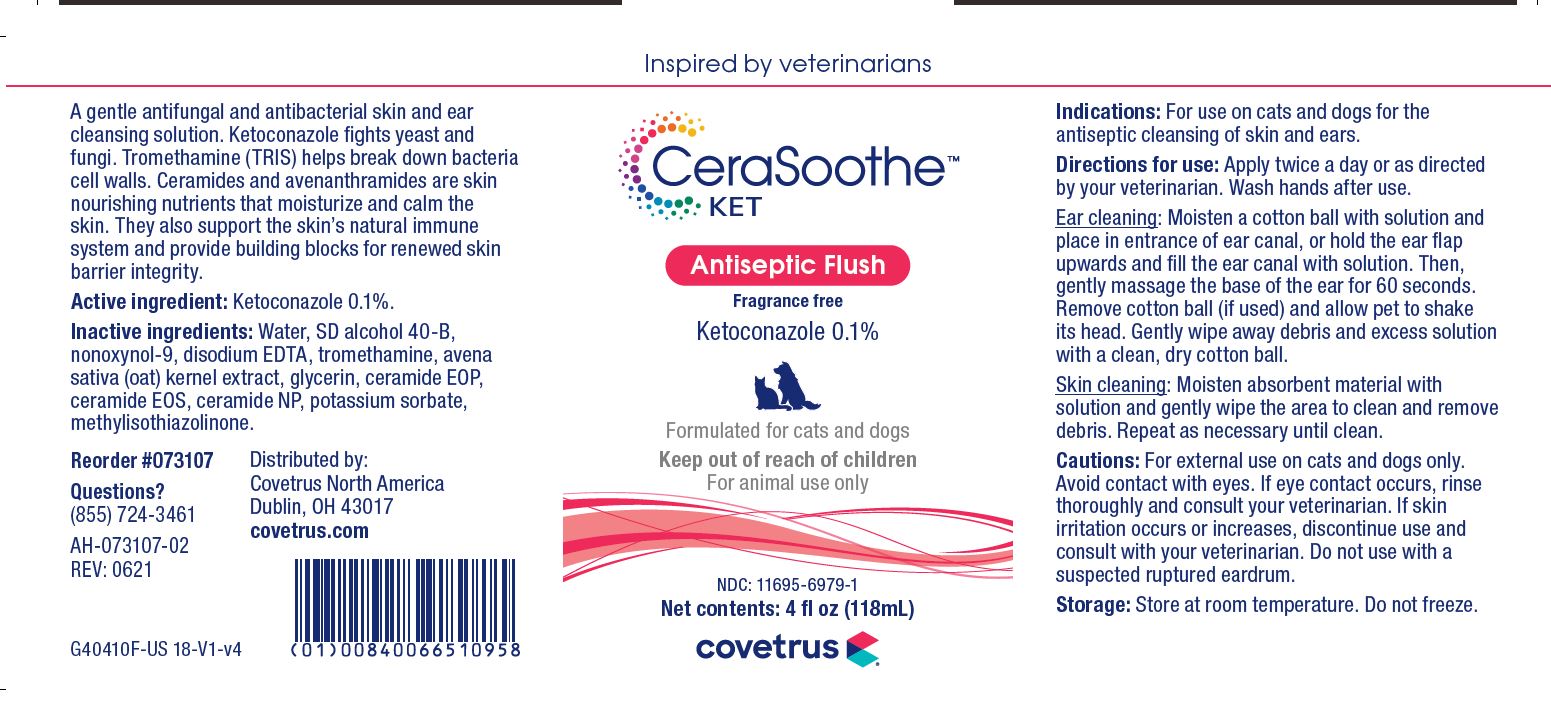 DRUG LABEL: CeraSoothe
NDC: 11695-6979 | Form: SOLUTION
Manufacturer: Butler Animal Health Supply, LLC dba Covetrus North America
Category: animal | Type: OTC ANIMAL DRUG LABEL
Date: 20220523

ACTIVE INGREDIENTS: KETOCONAZOLE 1 mg/1 mL
INACTIVE INGREDIENTS: WATER; ALCOHOL; NONOXYNOL-9; EDETATE DISODIUM; TROMETHAMINE; AVENANTHRAMIDES; GLYCERIN; CERAMIDE 1; CERAMIDE EOS; CERAMIDE NP; POTASSIUM SORBATE; METHYLISOTHIAZOLINONE

DESCRIPTION

CeraSoothe KET

Antiseptic Flush

Fragrance free

Ketoconazole 0.1%

Formulated for cats and dogs

Keep out of reach of children

For animal use only

A gentle antifungal and antibacterial skin and ear cleansing solution. Ketoconazole fights yeast and fungi. Tromethamine (TRIS) helps break down bacteria cell walls. Ceramides and avenanthramides are skin nourishing nutrients that moisturize and calm the skin. They also support the skin's natural immune system and provide building blocks for renewed skin barrier integrity.

Active ingredients: Ketoconazole 0.1%.

Inactive ingredients: Water, SD Alcohol 40-B, nonoxynol-9, disodium EDTA, tromethamine, avena sativa (oat) kernal extract, glycerin, ceramide EOP, ceramide EOS, ceramide NP, potassium sorbate, methylisothiazolinone.

INDICATIONS AND USAGE

Indications: For use on cats and dogs for the antiseptic cleansing of skin and ears.

Directions for use: Apply twice a day or as directed by your veterinarian. Wash hands after use.

Ear cleaning: Moisten a cotton ball with solution and place in entrance of ear canal, or hold the ear flap upwards and fill the ear canal with solution. Then, gently massage the base of the ear for 60 seconds. Remove cotton ball (if used) and allow pet to shake its head. Gently wipe away debris and excess solution with a clean, dry cotton ball.

Skin cleaning: Moisten absorbent material with solution and gently wipe the area to clean and remove debris. Repeat as necessary until clean.

PRECAUTIONS

Cautions: For external use on dogs or cats only. Avoid contact with the eyes. If eye contact occurs, rinse thoroughly and consult your veterinarian. If skin irritation occurs or increases, discontinue use and consult with your veterinarian. Do not use in the case of a suspected ruptured eardrum.

Storage: Store at room temperature. Do not freeze.

Questions?

(855) 724-3461

Distributed by:
Covetrus North America
Dublin, OH 43017
covetrus.com

PRINCIPAL DISPLAY PANEL - 4 OUNCE (118 mL) Bottle

Inspired by veterinarians

CeraSoothe KET

Antiseptic Flush

Fragrance free

Ketoconazole 0.1%,

Formulated for cats and dogs

Keep out of reach of children

For animal use only

NDC 11695-6979-1

Net contents: 4 fl oz (118 mL)

PRINCIPAL DISPLAY PANEL - 16 OUNCE (473 mL) Bottle

Inspired by veterinarians

CeraSoothe KET

Antiseptic Flush

Fragrance free

Ketoconazole 0.1%,

Formulated for cats and dogs

Keep out of reach of children

For animal use only

NDC 11695-6979-2

Net contents: 16 fl oz (473 mL)